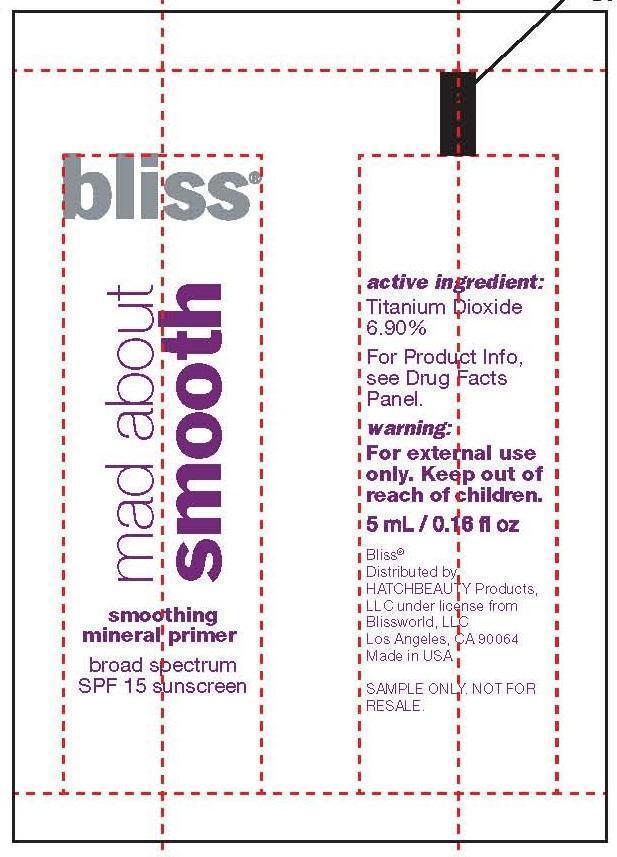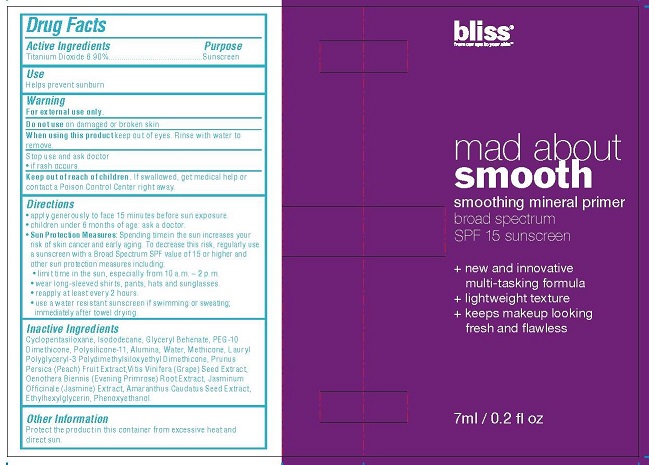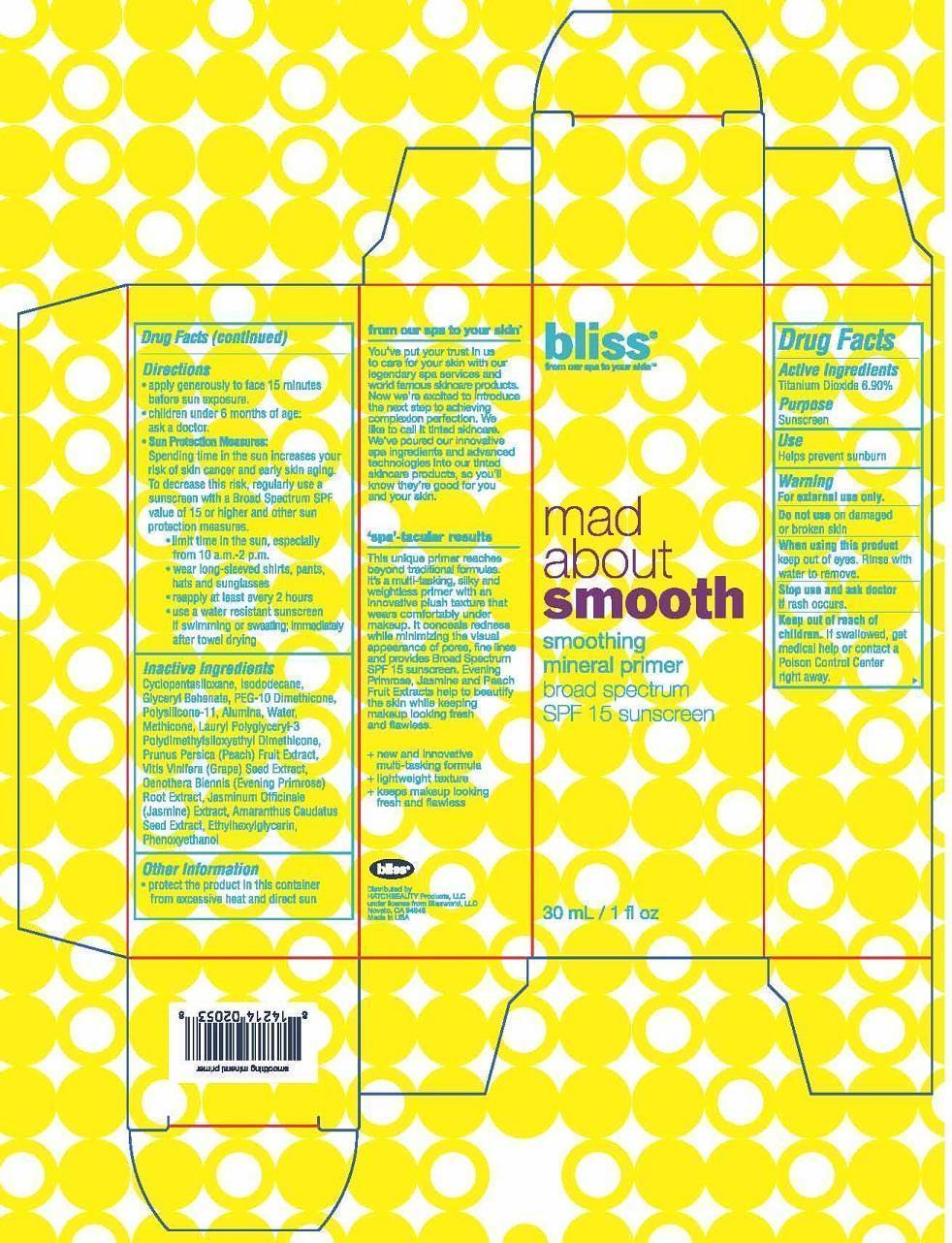 DRUG LABEL: SMOOTHING MINERAL PRIMER
NDC: 69863-101 | Form: LOTION
Manufacturer: HATCHBEAUTY PRODUCTS LLC
Category: otc | Type: HUMAN OTC DRUG LABEL
Date: 20151216

ACTIVE INGREDIENTS: TITANIUM DIOXIDE 6.90 g/100 mL
INACTIVE INGREDIENTS: CYCLOMETHICONE 5; ISODODECANE; GLYCERYL MONOBEHENATE; PEG-10 DIMETHICONE (600 CST); POLYSILICONE-15; ALUMINUM OXIDE; WATER; METHICONE (20 CST); LAURYL PEG-9 POLYDIMETHYLSILOXYETHYL DIMETHICONE; PEACH; VITIS VINIFERA SEED; OENOTHERA BIENNIS ROOT; JASMINUM OFFICINALE FLOWER; AMARANTHUS CAUDATUS SEED; ETHYLHEXYLGLYCERIN; PHENOXYETHANOL

ACTIVE INGREDIENTS

Titanium Dioxide 6.90%

PURPOSE

Sunscreen

USE

Helps prevent sunburn

WARNINGS

Warning
• For external use only.
• Do not use on damaged or broken skin

WHEN USING THIS PRODUCT

• Keep out of eyes. Rinse with water to remove.

STOP USE AND ASK DOCTOR

• If rash occurs.

• Keep out of reach of children. If product is swallowed, get medical help or contact a Poison Control Center right away.

DIRECTIONS

• Apply generously to face 15 minutes before sun exposure.

• Children under 6 months of age: ask a doctor.

Sun Protection Measures:

Spending time in the sun increases your risk of skin cancer and early skin aging. To decrease this risk, regularly use a sunscreen with a Broad Spectrum SPF value of 15 or higher and other sun protection measures.

• limit time in the sun, especially from 10 a.m.-2 p.m.

• wear long-sleeved shirts, pants, hats and sunglasses

• reapply at least every 2 hours

• use a water resistant sunscreen if swimming or sweating; immediately after towel drying

INACTIVE INGREDIENTS

Cyclopentasiloxane, Isododecane, Glyceryl Behenate, PEG-10 Dimethicone, Polysilicone-11, Alumina, Water, Methicone, Lauryl Polyglyceryl-3 Polydimethylsiloxyethyl Dimethicone, Prunus Persica (Peach) Fruit Extract, Vitis Vinifera (Grape) Seed Extract, Oenothera Biennis (Evening Primrose) Root Extract, Jasminum Officinale (Jasmine) Extract, Amaranthus Caudatus Seed Extract, Ethylhexylglycerin, Phenoxyethanol.

OTHER INFORMATION

• protect the product in this container from excessive heat and direct sun